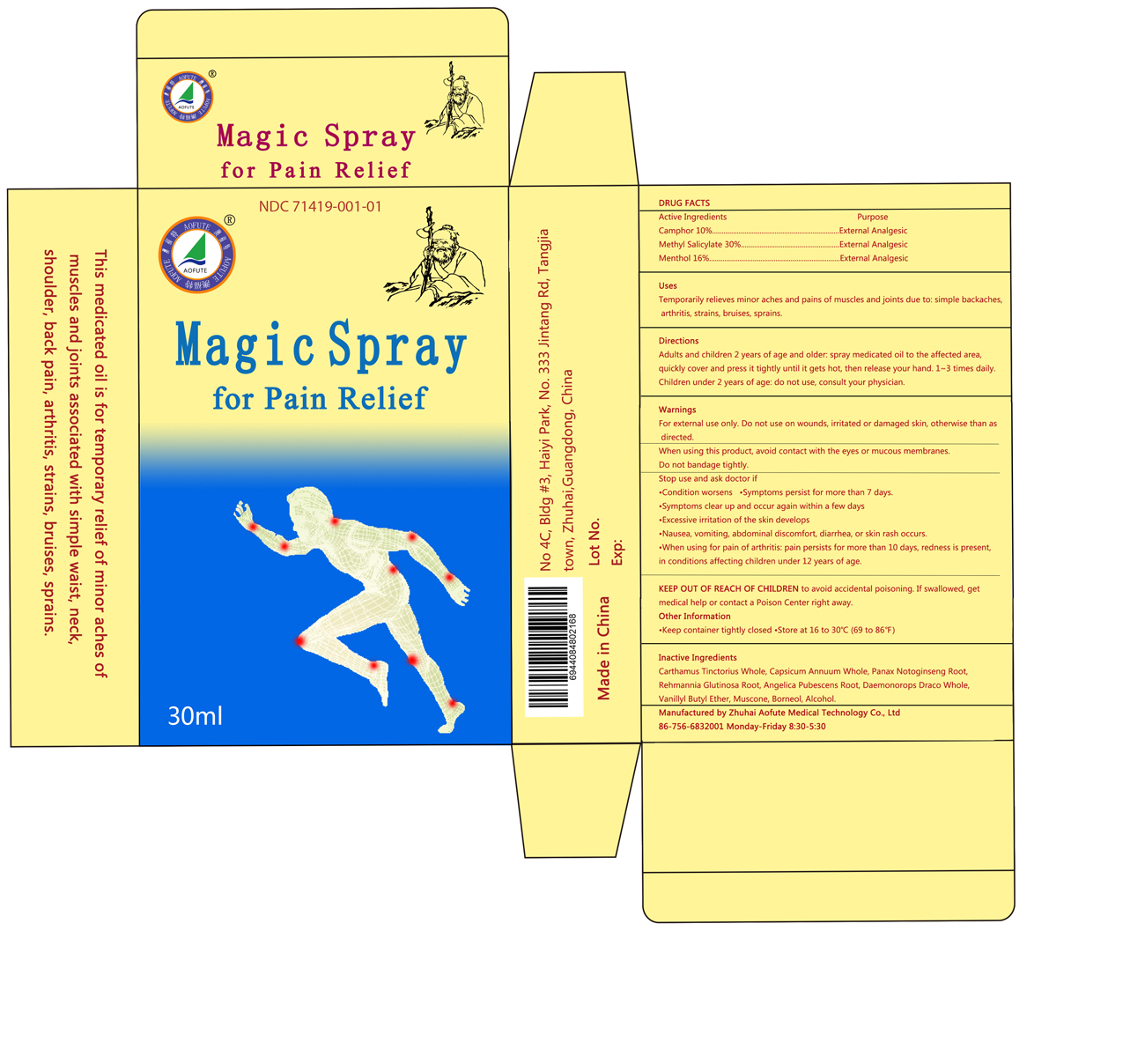 DRUG LABEL: Magic For Pain Relief
NDC: 71419-001 | Form: SPRAY
Manufacturer: Zhuhai Aofute Medical Technology Co, Ltd
Category: otc | Type: HUMAN OTC DRUG LABEL
Date: 20201207

ACTIVE INGREDIENTS: CAMPHOR (SYNTHETIC) 10 g/100 mL; METHYL SALICYLATE 30 g/100 mL; MENTHOL 16 g/100 mL
INACTIVE INGREDIENTS: CARTHAMUS TINCTORIUS WHOLE; CAPSICUM ANNUUM WHOLE; PANAX NOTOGINSENG ROOT; REHMANNIA GLUTINOSA ROOT; ANGELICA PUBESCENS ROOT; DAEMONOROPS DRACO WHOLE; VANILLYL BUTYL ETHER; MUSCONE; BORNEOL; ALCOHOL

Zhuhai Aofute Medical Technology Co, Ltd

Active Ingredients

Camphor 10%

Methyl Salicylate 30%

Menthol 16%

Purpose

Camphor External Analgesic

Methyl Salicylate External Analgesic

Menthol External Analgesic

Uses

Temporarily relieves minor aches and pains of muscles and joints due to: simple backaches, arthritis, strains, bruises, sprains

Directions

Adults and children 2 years of age and older: spray medicated oil to the affected area, quickly cover and press it tightly until it gets hot, then release your hand, 1 to 3 times daily. Children under 2 years of age: Do not use, consult your physician.

Warnings

For external use only. Do not use on wounds, irritated or damaged skin, otherwise than as directed.

When Using This Product

Avod contact with the eyes or mucous membranes. Do not bandage tightly.

Stop Use and Ask a Doctor If

Condition worsens

Symptoms persist for more than 7 days

Symptoms clear up and occur again within a few days

Excessive irritation of the skin develops

Nausea, vomiting, abdominal discomfort, diarrhea, or skin rash occurs

When using for pain of arthritis: pain persists for more than 10 days, redness is present, in conditions affecting children 12 years of age.

Keep out of reach of children to avoid accidental poisoning. If swallowed, get medical help or contact Poison Control Center right away.

Other Information

Keep container tightly closed. Store at 16 to 30°C (69 to 86°F) and keep away from direct sunlight.

Inactive Ingredients

CARTHAMUS TINCTORIUS WHOLE, CAPSICUM ANNUUM WHOLE, PANAX NOTOGINSENG ROOT, REHMANNIA GLUTINOSA ROOT, ANGELICA PUBESCENS ROOT, DAEMONOROPS DRACO WHOLE, VANILLYL BUTYL ETHER, MUSCONE, BORNEOL, ALCOHOL